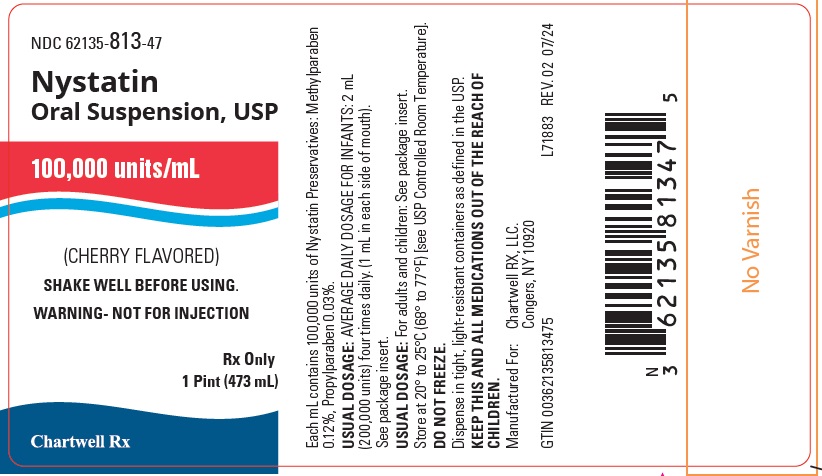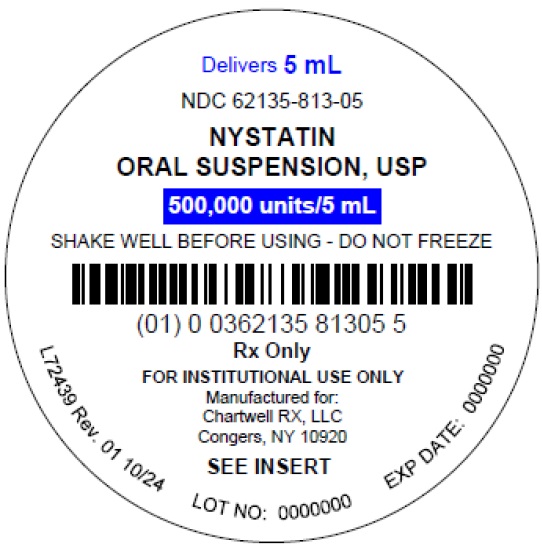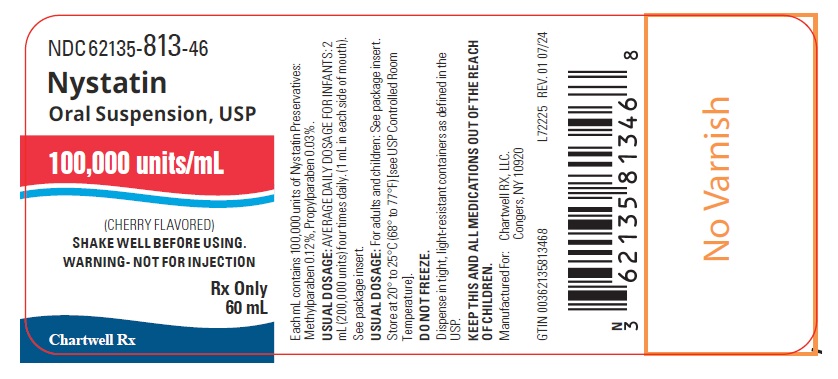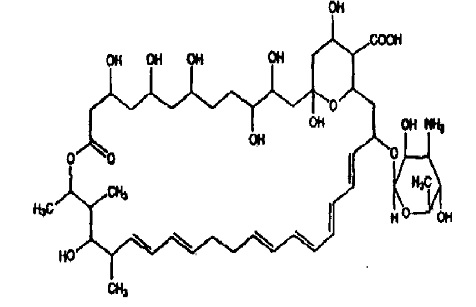 DRUG LABEL: Nystatin
NDC: 62135-813 | Form: SUSPENSION
Manufacturer: Chartwell RX, LLC
Category: prescription | Type: HUMAN PRESCRIPTION DRUG LABEL
Date: 20260129

ACTIVE INGREDIENTS: NYSTATIN 100000 U/1 mL
INACTIVE INGREDIENTS: EDETATE CALCIUM DISODIUM; HYDROCHLORIC ACID; METHYLPARABEN; POLYSORBATE 80; PROPYLPARABEN; BENTONITE; SODIUM HYDROXIDE; SUCROSE; D&C YELLOW NO. 10; WATER

Nystatin Oral Suspension, USP

DESCRIPTION

Nystatin, USP is obtained from Streptomyces noursei. It is known to be a mixture, but the composition has not been completely elucidated. Nystatin A is closely related to amphotericin B. Each is a macro-cyclic lactone containing a ketal ring, an all-transpolyene system, and a mycosamine (3-amino-3-deoxyrhamose) moiety.

Its structural formula is:

C47H75NO17 M.W .926 .13

Nystatin Oral Suspension, USP, is a cherry-flavored, ready-to-use suspension containing 100,000 units of Nystatin, USP per mL. Nystatin, USP contains the following inactive ingredients: artificial (wild) cherry flavor, D&C Yellow 10, edetate calcium disodium, hydrochloric acid, methylparaben, polysorbate 80, propylparaben, purified bentonite, purified water, sodium hydroxide and sucrose.

CLINICAL PHARMACOLOGY

Nystatin acts by binding to sterols in the cell membrane of the fungus with a resultant change in membrane permeability allowing leakage of intracellular components. Nystatin is absorbed very sparingly following oral administration, with no detectable blood levels when given in the recommended doses.

INDICATIONS AND USAGE

Nystatin oral suspension is indicated for the treatment of infections of the oral cavity caused by Candida albicans.

CONTRAINDICATIONS

Nystatin is contraindicated in patients with a history of hypersensitivity to nystatin or any of the suspension components.

PRECAUTIONS

General

Discontinue treatment with nystatin if sensitization or irritation is reported during use.

Nystatin is not effective in the treatment of systemic mycoses since it is not significantly absorbed from the gastrointestinal tract.

Information for the Patient

Patient should be advised to retain nystatin in the mouth as long as possible and to continue its use for at least 2 days after symptoms have subsided.

There should be no interruption or discontinuation of the medication until the prescribed course of treatment is completed, even though symptomatic relief may occur within a few days.

If symptoms of local irritation develop, the physician should be notified immediately.

Laboratory Tests

If there is a lack of therapeutic response, appropriate microbiological studies (e.g., KOH smears and/or cultures) should be repeated to confirm the diagnosis of candidiasis and rule out other pathogens before instituting another course of therapy.

Carcinogenesis, Mutagenesis, Impairment of Fertility

No long-term animal studies have been performed to evaluate the carcinogenic potential of nystatin. In mice exposed to nystatin 50 mg/kg by injection, an increased incidence of chromosomal aberrations, consisting primarily of chromatid breaks, was observed in bone marrow cells. However, there have been no studies to determine the mutagenicity of orally-administered nystatin or its effects on fertility in males or females.

Pregnancy

Teratogenic effects

Teratogenicity studies have not been conducted with nystatin. It is also not known whether nystatin can cause fetal harm when administered to a pregnant woman or can affect reproduction capacity. Nystatin should be given to a pregnant woman only if clearly needed.

Nonteratogenic effects

In one rat reproductive study, nystatin was administered orally to pregnant rats in single doses of 100, 500, or 3000 mg/kg on the ninth day of gestation, or as multiple doses of 500 mg/kg/day on gestation days 1-20, 1-4, 7-10, 11-14, or 15-18. It was found that nystatin had a slight abortive effect when used during the whole period of pregnancy. No abnormalities were seen in surviving fetuses. Although no adverse effects or complications have been attributed to the use of intra-vaginal nystatin in neonates born to women treated during pregnancy, no similar studies evaluating complications of oral nystatin have been conducted.

Nursing Mothers

It is not known whether nystatin is excreted in human milk. Because many drugs are excreted in human milk, caution should be exercised when nystatin is administered to a nursing woman.

Pediatric Use

See DOSAGE AND ADMINISTRATIONsection for pediatric dosing recommendations.

ADVERSE REACTIONS

Gastrointestinal symptoms including diarrhea, gastrointestinal distress, nausea, vomiting and burning of the mouth have been reported. Hypersensitivity reactions including rash, pruritus, and anaphylactoid reaction have also been reported.

OVERDOSAGE

Oral doses of nystatin in excess of five million units daily have caused nausea and gastrointestinal upset.

DOSAGE AND ADMINISTRATION

Infants: 2 mL (200,000 units) four times daily (1 mL in each side of mouth).

Pediatric patients and adults: 4 to 6 mL (400,000 to 600,000 units) four times daily (one-half of dose in each side of mouth).

NOTE: Limited clinical studies in neonates, including premature and low-birth weight neonates, indicate that 1 mL (100,000 units) four times daily is effective.

Local treatment should be continued at least 48 hours after perioral symptoms have disappeared and/or cultures returned to normal. It is recommended that the drug be retained in the mouth as long as possible before swallowing.

HOW SUPPLIED

Nystatin Oral Suspension, USP is a bright yellow color suspension with cherry flavor containing 100,000 units of nystatin per mL, supplied as follows:

NDC 62135-813-46 – bottle of 60 mL

NDC 62135-813-47 – bottle of 473 mL

NDC 62135-813-05 – 5 mL Unit Dose Cups

NDC 62135-813-24 – 20 Unit Dose Cups of 5 mL each

Store at controlled room temperature between 20°C to 25°C (68°F to 77°F).

DO NOT FREEZE

Manufactured for:
Chartwell RX, LLC.
Congers, NY 10920

L71884

Rev. 01/2026

PRINCIPAL DISPLAY PANEL

Nystatin Oral Suspension, USP 100,000 units/mL - NDC 62135-813-46 - 60 ml Bottle Label

Nystatin Oral Suspension, USP 100,000 units/mL - NDC 62135-813-47 - 1 Pint (473 mL) Bottle Label

Nystatin Oral Suspension, USP 500,000 units/5mL - NDC 62135-813-05 – 5 mL Unit Dose Label